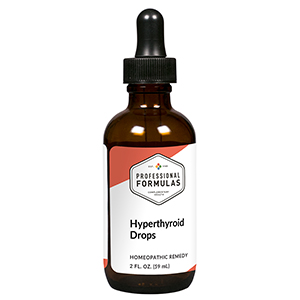 DRUG LABEL: Hyperthyroid Drops
NDC: 63083-2029 | Form: LIQUID
Manufacturer: Professional Complementary Health Formulas
Category: homeopathic | Type: HUMAN OTC DRUG LABEL
Date: 20190815

ACTIVE INGREDIENTS: POTASSIUM IODIDE 2 [hp_X]/59 mL; LYCOPUS VIRGINICUS WHOLE 2 [hp_X]/59 mL; APIS MELLIFERA 3 [hp_X]/59 mL; ACTIVATED CHARCOAL 3 [hp_X]/59 mL; SPONGIA OFFICINALIS SKELETON, ROASTED 4 [hp_X]/59 mL; CONIUM MACULATUM FLOWERING TOP 6 [hp_X]/59 mL; PHOSPHORUS 6 [hp_X]/59 mL; BOS TAURUS PITUITARY GLAND, POSTERIOR 6 [hp_X]/59 mL; LACHESIS MUTA VENOM 8 [hp_X]/59 mL
INACTIVE INGREDIENTS: ALCOHOL; WATER

C29

ACTIVE INGREDIENTS

Kali iodatum 2X
Lycopus virginicus 2X, 6X, 12X
Apis mellifica 3X
Carbo vegetabilis 3X
Spongia tosta 4X
Conium maculatum 6X
Phosphorus 6X
Pituitary 6X
Lachesis mutus 8X

QUESTIONS

Professional Formulas

PO Box 2034 Lake Oswego, OR 97035

INDICATIONS

For the temporary relief of unexpected weight loss, excessive hunger, sweating, irritability or nervousness, heat intolerance, or insomnia.*

PURPOSE

*Claims based on traditional homeopathic practice, not accepted medical evidence. Not FDA evaluated.

WARNINGS

Consult a doctor if condition worsens or if symptoms persist. Keep out of the reach of children. In case of overdose, get medical help or contact a poison control center right away. If pregnant or breastfeeding, ask a healthcare professional before use.

Keep out of the reach of children.

PREGNANCY OR BREAST FEEDING

If pregnant or breastfeeding, ask a healthcare professional before use.

DIRECTIONS

Place drops under tongue 30 minutes before/after meals. Adults and children 12 years and over: Take 10 drops up to 3 times per day. Consult a physician for use in children under 12 years of age.

OTHER INFORMATION

Tamper resistant. If seal is broken, do not use. After opening, close container tightly and store at room temperature away from heat.

INACTIVE INGREDIENTS

20% ethanol, purified water.

LABEL

Est 1985

Professional Formulas

Complementary Health

Hyperthyroid Drops

Homeopathic Remedy

2 FL. OZ. (59 mL)